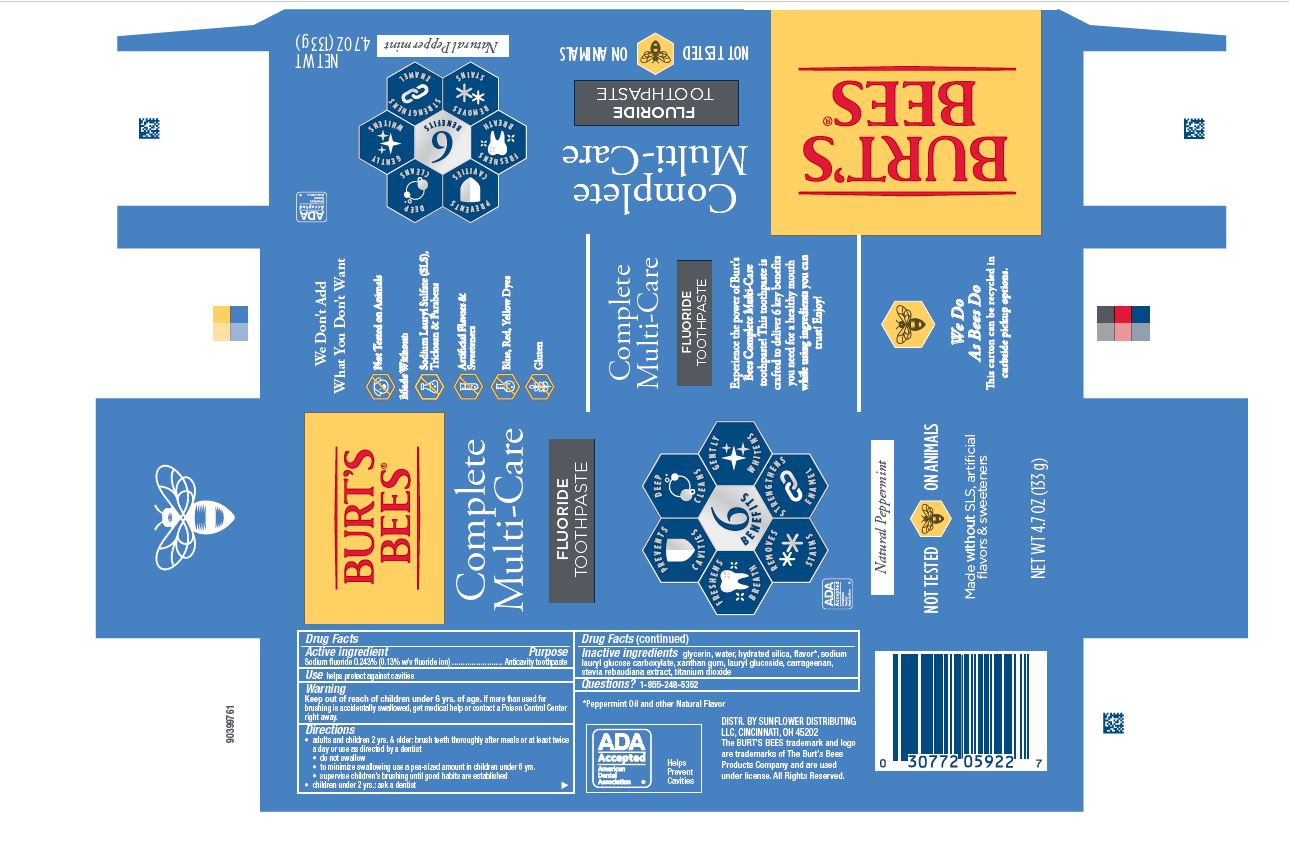 DRUG LABEL: Burts Bees
NDC: 69423-835 | Form: PASTE, DENTIFRICE
Manufacturer: Procter & Gamble Manufacturing Company
Category: otc | Type: HUMAN OTC DRUG LABEL
Date: 20260202

ACTIVE INGREDIENTS: SODIUM FLUORIDE 1.3 mg/1 g
INACTIVE INGREDIENTS: LAURYL GLUCOSIDE; CARRAGEENAN; XANTHAN GUM; WATER; HYDRATED SILICA; GLYCERIN; STEVIA REBAUDIANA WHOLE; SODIUM LAURYL GLYCOL CARBOXYLATE; TITANIUM DIOXIDE

Burt's Bees Complete Multi-Care Fluoride Toothpaste Natural Peppermint

Drug Facts

Active ingredient

Sodium fluoride 0.243% (0.13% w/v fluoride ion)

Purpose

Anticavity toothpaste

Use

helps protect against cavities

Warnings

Keep out of reach of children under 6 yrs of age.If more than used for brushing is accidentally swallowed, get medical help or contact a Poison Control Center right away.

Directions

- adults and children 2 yrs. & older: brush teeth thoroughly after meals or at least twice a day or use as directed by a dentist
- do not swallow
- to minimize swallowing use a pea-sized amount in children under 6
- supervise children’s brushing until good habits are established
- children under 2 yrs.: ask a dentist

Inactive ingredients

glycerin, water, hydrated silica, flavor*, sodium
lauryl glucose carboxylate, xanthan gum, lauryl glucoside, carrageenan,
stevia rebaudiana extract, titanium dioxide

Questions?

1-855-248-5352

*Peppermint Oil and other Natural Flavor

DISTR. BY SUNFLOWER DISTRIBUTING
LLC, CINCINNATI, OH 45202

PRINCIPAL DISPLAY PANEL - 133 g tube in carton

BURT'S

BEES®

Complete

Multi-Care

FLUORIDE

Toothpaste

Prevents Cavities

Deep Cleans

Freshens Breath

6 Benefits

Gently Whitens

Removes Stains

Strengthens Enamel
ADA

Accepeted

American

Dental

Association

Natural Peppermint

NOT TESTE4D ON ANIMALS

Made without SLS,

artificial flavors & sweetners

NET WT 4.7 OZ (133 g)